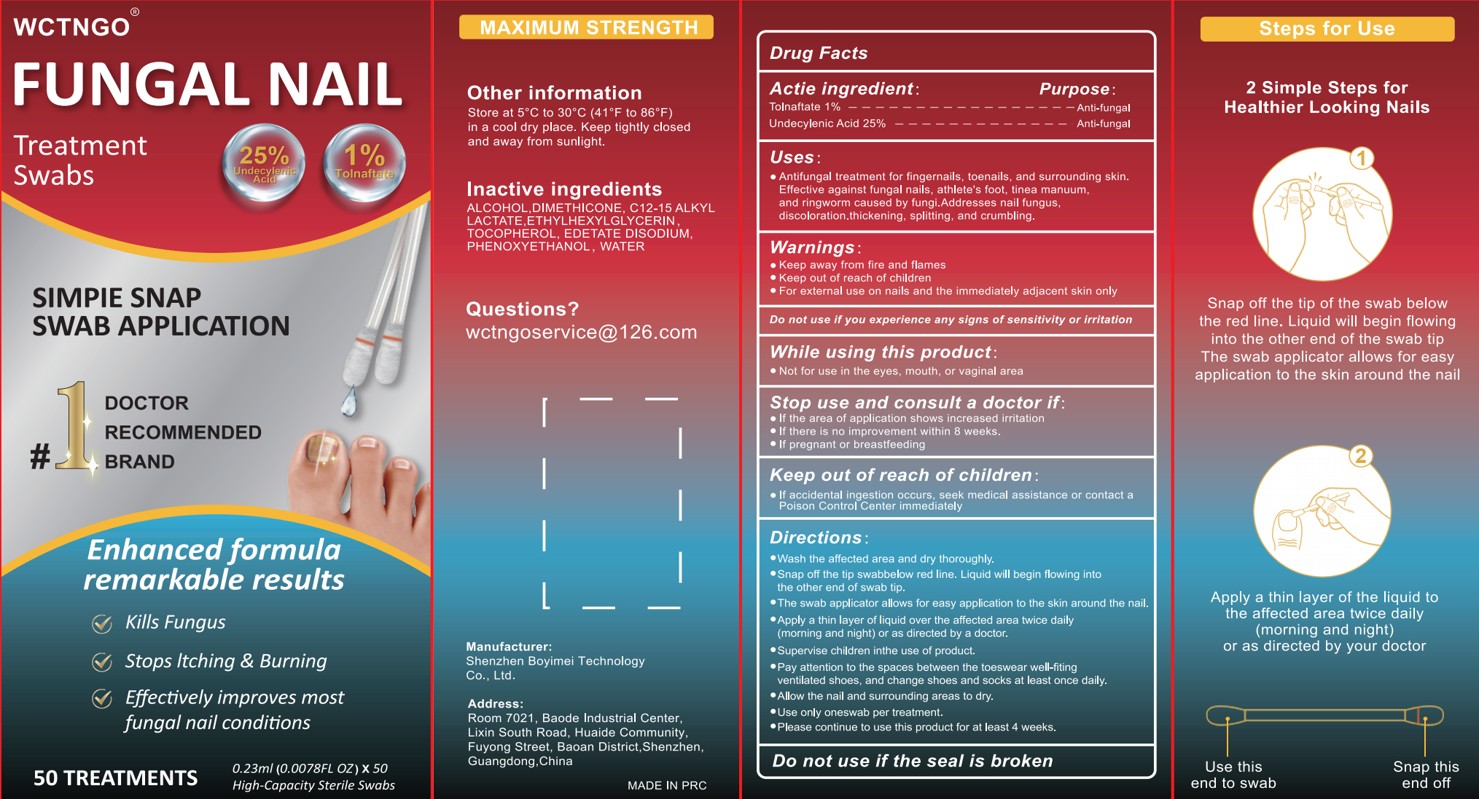 DRUG LABEL: WCTNGO  Fungal Nail Treatment Swabs
NDC: 85992-003 | Form: LIQUID
Manufacturer: Shenzhen Boyimei Technology Co., Ltd.
Category: otc | Type: HUMAN OTC DRUG LABEL
Date: 20250806

ACTIVE INGREDIENTS: TOLNAFTATE 1 g/100 mL; UNDECYLENIC ACID 25 g/100 mL
INACTIVE INGREDIENTS: C12-15 ALKYL LACTATE; ALCOHOL; WATER; EDETATE DISODIUM; ETHYLHEXYLGLYCERIN; PHENOXYETHANOL; DIMETHICONE; TOCOPHEROL

85992-003 WCTNGO Fungal Nail Treatment Swabs

ACTIVE INGREDIENT

Tolnaftate 1%
Undecylenic Acid 25%

PURPOSE

Anti-fungal

INDICATIONS AND USAGE

Antifungal treatment for fingernails, toenails, and surrounding skin.Effective against fungal nails, athlete's foot, tinea manuum,and ringworm caused by fungi.Addresses nail fungus,discoloration.thickening,splitting, and crumbling.

WARNINGS

Keep away from fire and flames
Keep out of reach of children
For external use on nails and the immediately adjacent skin only

Do not use ifyou experience any signs ofsensitivity or irritation

WHEN USING

Not for use in the eyes, mouth, or vaginal area

STOP USE

If the area of application shows increased irritation
If there is no improvement within 8 weeks
If pregnant or breastfeeding

KEEP OUT OF REACH OF CHILDREN

If accidental ingestion occurs, seek medical assistance or contact a
Poison Control Center immediately

DOSAGE AND ADMINISTRATION

Wash the affected area and dry thoroughly.
Snap off the tip swabbelow red line. Liquid will begin flowing into the other end of swab tip.
The swab applicator allows for easy application to the skin around the nail.
Apply a thin layer of liquid over the affected area twice daily(morning and night) or as directed by a doctor.
Supervise children inthe use of product.
Pay attention to the spaces between the toeswear well-fitingventilated shoes, and change shoes and socks at least once dailye
Allow the nail and surrounding areas to dry.
Use only oneswab per treatment.
Please continue to use this product for at least 4 weeks.

INACTIVE INGREDIENT

ALCOHOL,DIMETHICONE, C12-15 ALKYLLACTATE.ETHYLHEXYLGLYCERIN.TOCOPHEROL,EDETATE DISODIUM.PHENOXYETHANOL，WATER